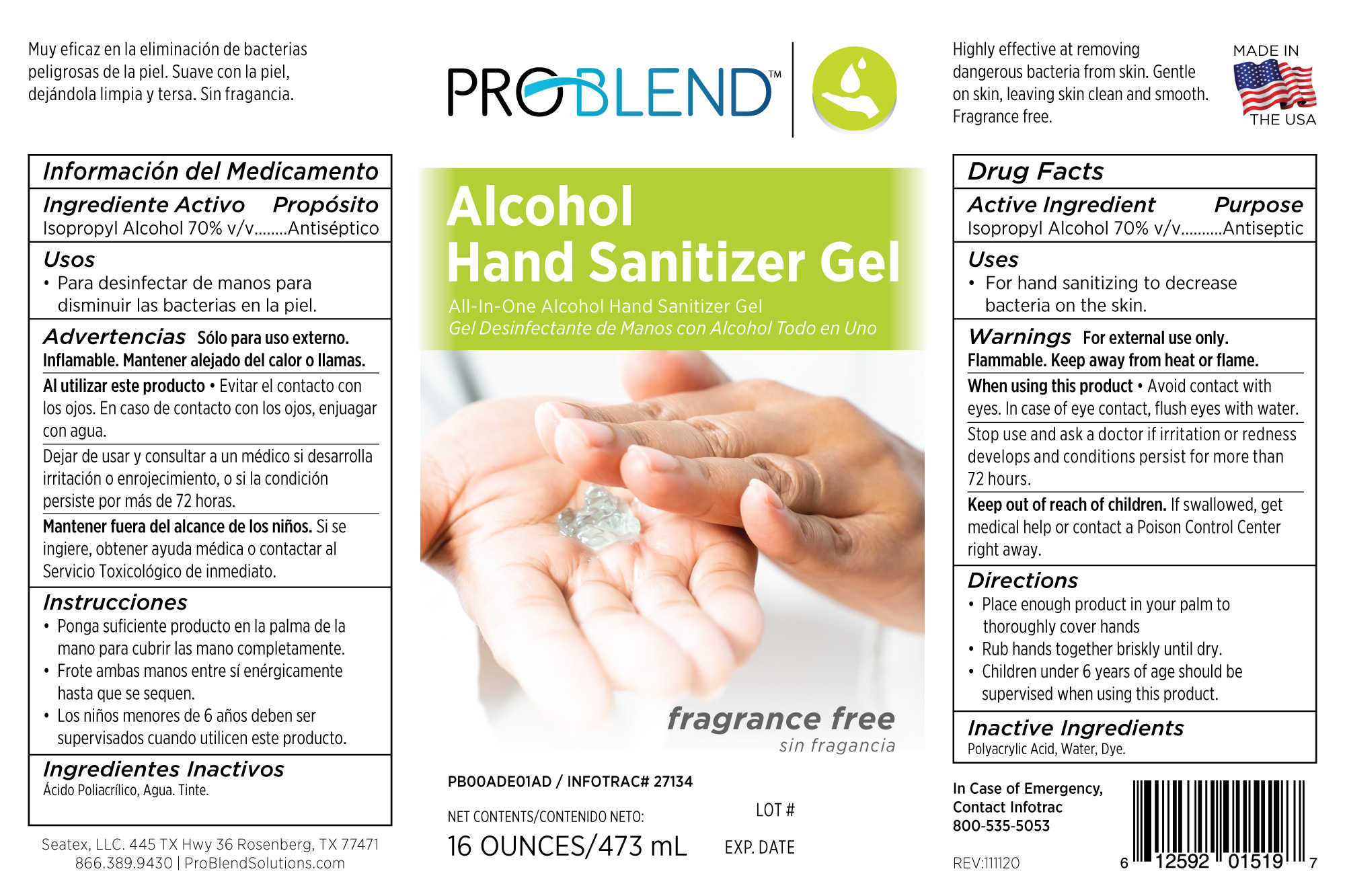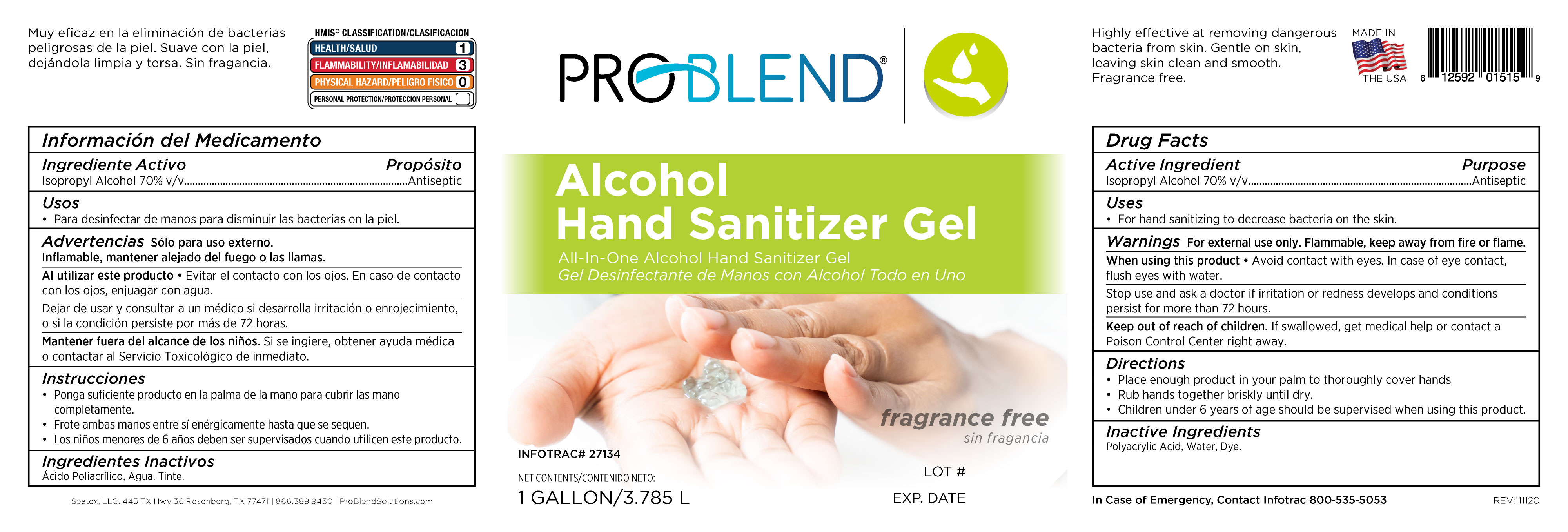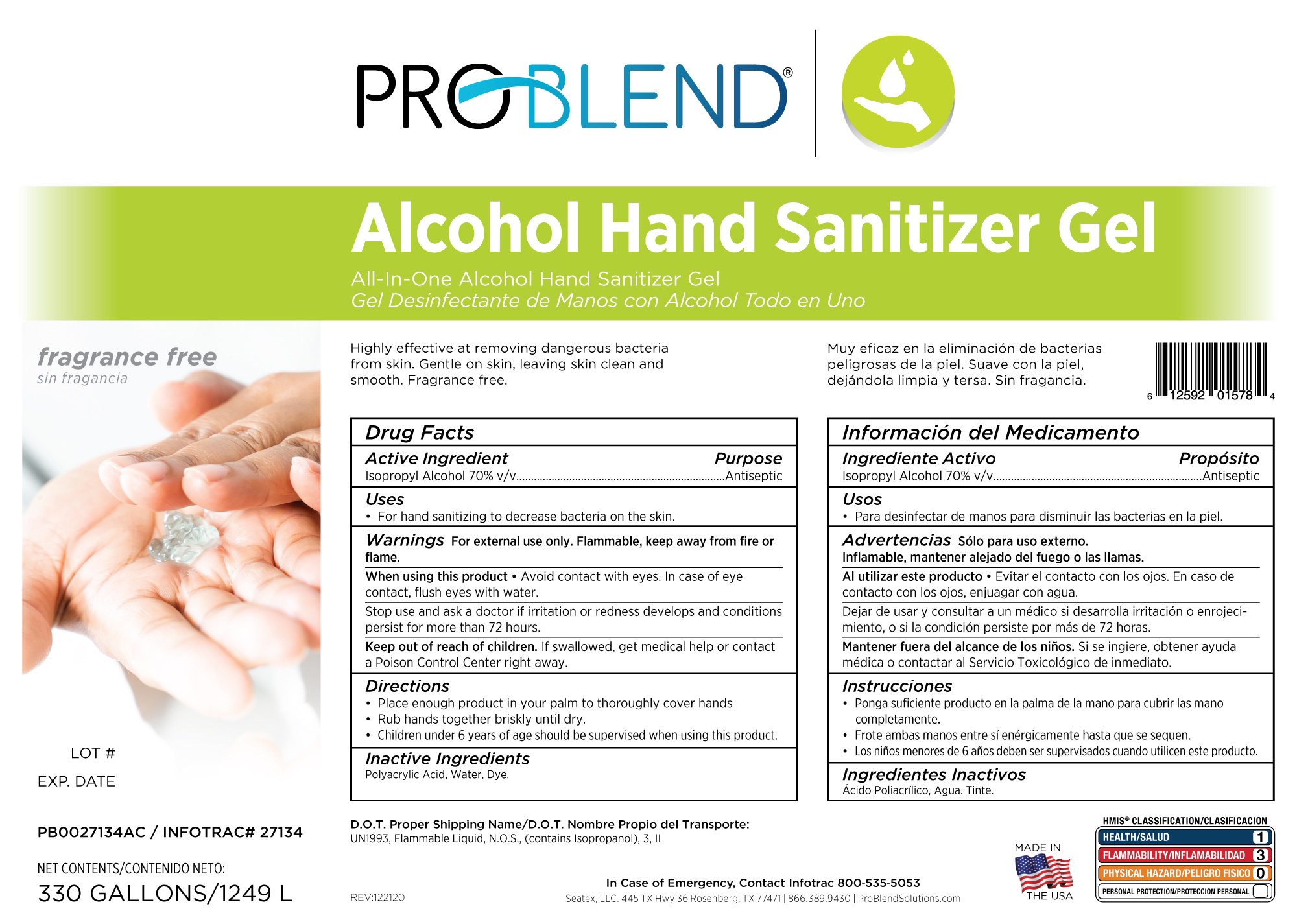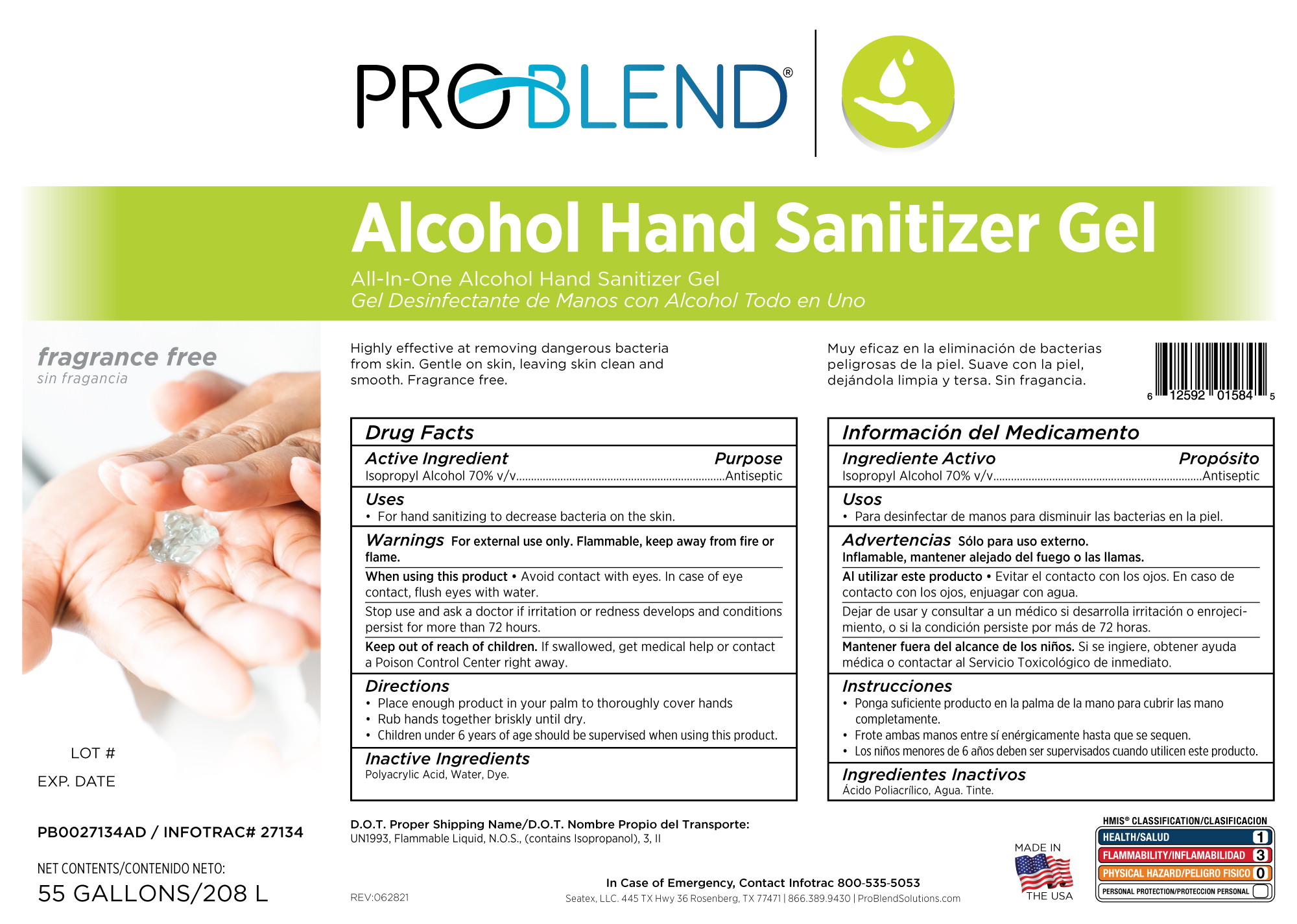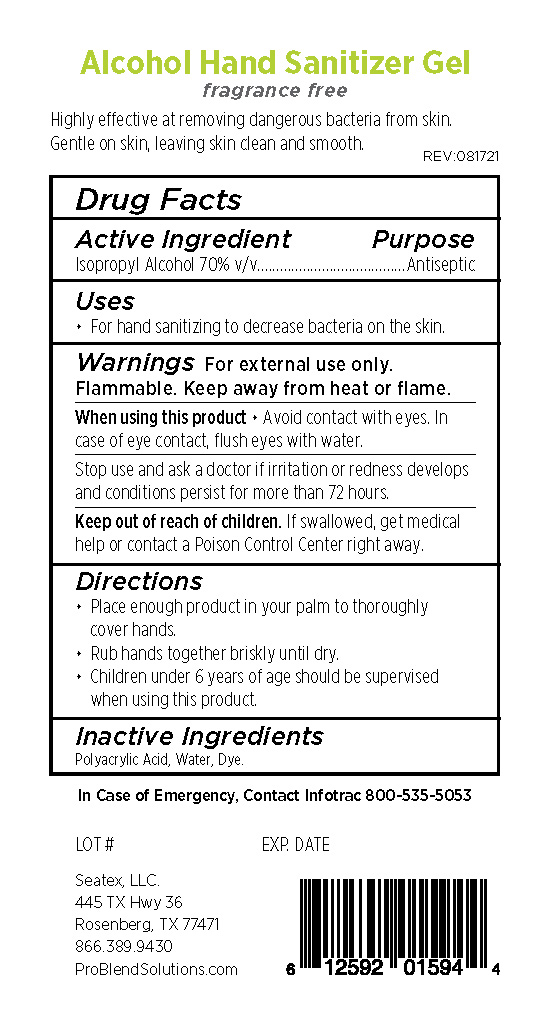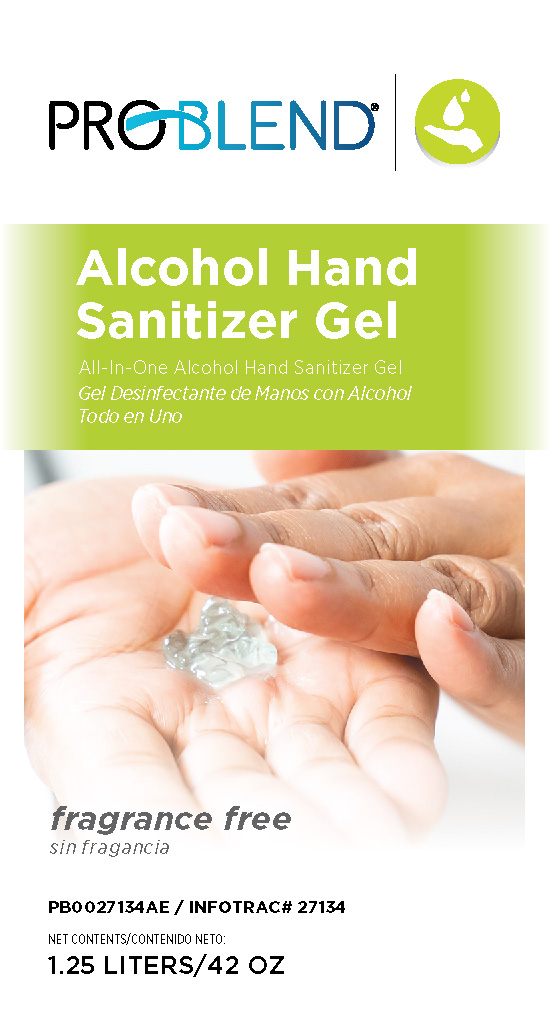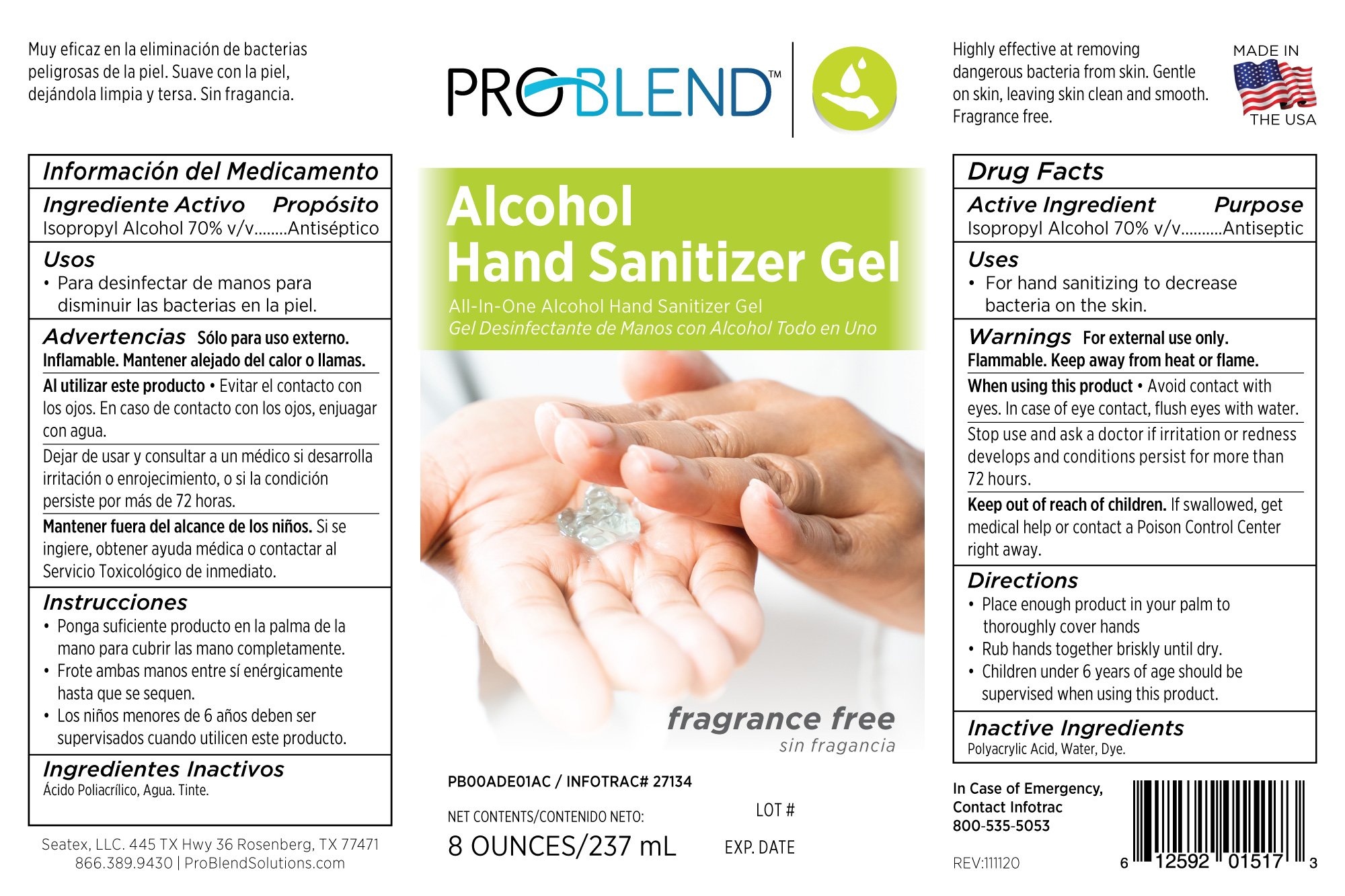 DRUG LABEL: Problend Alcohol Hand Sanitizer Gel
NDC: 76250-134 | Form: GEL
Manufacturer: Seatex, LLC
Category: otc | Type: HUMAN OTC DRUG LABEL
Date: 20220919

ACTIVE INGREDIENTS: ISOPROPYL ALCOHOL 70 mL/100 mL
INACTIVE INGREDIENTS: FD&C YELLOW NO. 5; WATER; RAPIDGEL EZ1; FD&C BLUE NO. 1

27134 IPA Hand Rapid Gel

Active Ingredient Purpose

Isopropyl Alcohol 70% v/v..........Antiseptic

PURPOSE

Antiseptic, Hand Sanitizer

Uses

For hand sanitizing to decrease bacteria on the skin.

Warnings For external use only.

Flammable. Keep away from heat or flame.

When using this product Avoid contact with

eyes. In case of eye contact, flush eyes with water.

Stop use and ask a doctor if irritation or redness

develops and conditions persist for more than

72 hours.

Keep out of reach of children. If swallowed, get

medical help or contact a Poison Control Center

right away.

Directions

Place enough product in your palm to

thoroughly cover hands

Rub hands together briskly until dry.

Children under 6 years of age shoud be

supervised when using this product.

Inactive Ingredients

Polyacrylic Acid, Water, Dye

PACKAGE LABEL

237 ml 76250-134-08

PACKAGE LABEL

473 mL 76250-134-16

PACKAGE LABEL

3.785 L 76250-134-01

PACKAGE LABEL

1249 L 76250.134-33

PACKAGE LABEL

1.25 L Front 76250-134-25

PACKAGE LABEL

1.25 L Back 76250-134-25